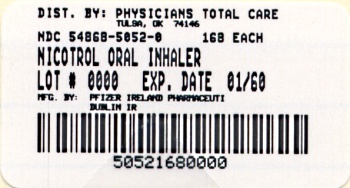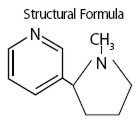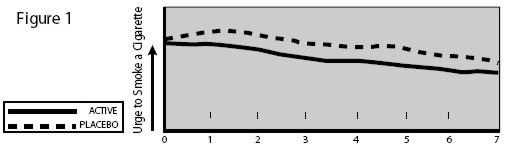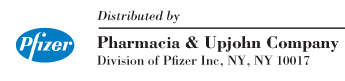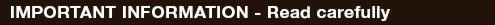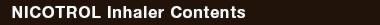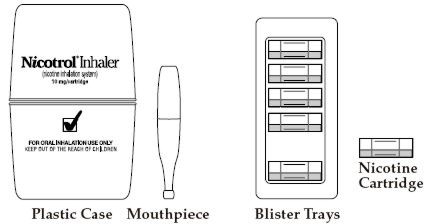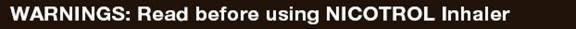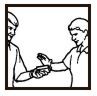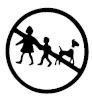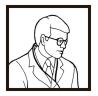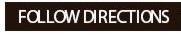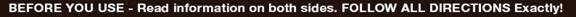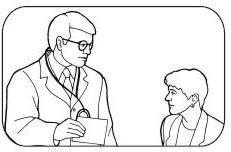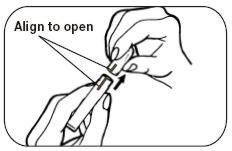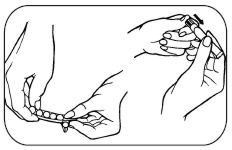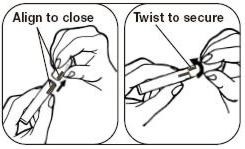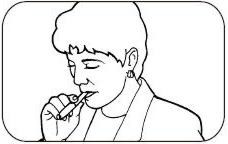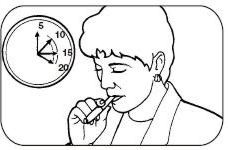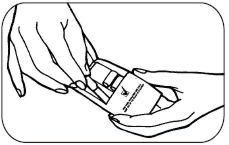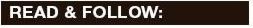 DRUG LABEL: NICOTROL
NDC: 54868-5052 | Form: INHALANT
Manufacturer: Physicians Total Care, Inc.
Category: prescription | Type: HUMAN PRESCRIPTION DRUG LABEL
Date: 20091210

ACTIVE INGREDIENTS: NICOTINE 4 mg/1 1
INACTIVE INGREDIENTS: MENTHOL

Nicotrol® Inhaler
(nicotine inhalation system)
10 mg per cartridge
(4 mg delivered)

DESCRIPTION

NICOTROL® Inhaler (nicotine inhalation system) consists of a mouthpiece and a plastic cartridge delivering 4 mg of nicotine from a porous plug containing 10 mg nicotine. The cartridge is inserted into the mouthpiece prior to use. Nicotine is a tertiary amine composed of a pyridine and a pyrrolidine ring. It is a colorless to pale yellow, freely water-soluble, strongly alkaline, oily, volatile, hygroscopic liquid obtained from the tobacco plant. Nicotine has a characteristic pungent odor and turns brown on exposure to air or light. Of its two stereoisomers, S(-)nicotine is the more active. It is the prevalent form in tobacco, and is the form in the NICOTROL Inhaler. The free alkaloid is absorbed rapidly through skin, mucous membranes, and the respiratory tract.

Chemical Name: S-3-(1-methyl-2-pyrrolidinyl) pyridine

Molecular Formula: C10H14N2

Molecular Weight: 162.23

Ionization Constants: pKa1 = 7.84, pKa2 = 3.04 at 15°C

Octanol-Water Partition Coefficient: 15:1 at pH 7

Nicotine is the active ingredient; inactive components of the product are menthol and a porous plug which are pharmacologically inactive. Nicotine is released when air is inhaled through the Inhaler.

CLINICAL PHARMACOLOGY

Pharmacologic Action

Nicotine, the chief alkaloid in tobacco products, binds stereo-selectively to nicotinic-cholinergic receptors at the autonomic ganglia, in the adrenal medulla, at neuromuscular junctions, and in the brain. Two types of central nervous system effects are believed to be the basis of nicotine's positively reinforcing properties. A stimulating effect is exerted mainly in the cortex via the locus ceruleus and a reward effect is exerted in the limbic system. At low doses the stimulant effects predominate while at high doses the reward effects predominate. Intermittent intravenous administration of nicotine activates neurohormonal pathways, releasing acetylcholine, norepinephrine, dopamine, serotonin, vasopressin, beta-endorphin, growth hormone, and ACTH.

Pharmacodynamics

The cardiovascular effects of nicotine include peripheral vasoconstriction, tachycardia, and elevated blood pressure. Acute and chronic tolerance to nicotine develops from smoking tobacco or ingesting nicotine preparations. Acute tolerance (a reduction in response for a given dose) develops rapidly (less than 1 hour), but not at the same rate for different physiologic effects (skin temperature, heart rate, subjective effects). Withdrawal symptoms such as cigarette craving can be reduced in most individuals by plasma nicotine levels lower than those from smoking.

Withdrawal from nicotine in addicted individuals can be characterized by craving, nervousness, restlessness, irritability, mood lability, anxiety, drowsiness, sleep disturbances, impaired concentration, increased appetite, minor somatic complaints (headache, myalgia, constipation, fatigue), and weight gain. Nicotine toxicity is characterized by nausea, abdominal pain, vomiting, diarrhea, diaphoresis, flushing, dizziness, disturbed hearing and vision, confusion, weakness, palpitations, altered respiration and hypotension.

Both smoking and nicotine can increase circulating cortisol and catecholamines, and tolerance does not develop to the catecholaminereleasing effects of nicotine. Changes in the response to a concomitantly administered adrenergic agonist or antagonist should be watched for when nicotine intake is altered during NICOTROL Inhaler therapy and/or smoking cessation (See PRECAUTIONS, Drug Interactions).

PHARMACOKINETICS

Absorption

Most of the nicotine released from the NICOTROL Inhaler is deposited in the mouth. Only a fraction of the dose released, less than 5%, reaches the lower respiratory tract. An intensive inhalation regimen (80 deep inhalations over 20 minutes) releases on the average 4 mg of the nicotine content of each cartridge of which about 2 mg is systemically absorbed. Peak plasma concentrations are typically reached within 15 minutes of the end of inhalation.

Absorption of nicotine through the buccal mucosa is relatively slow and the high and rapid rise followed by the decline in nicotine arterial plasma concentrations seen with cigarette smoking are not achieved with the inhaler. After use of the single inhaler the arterial nicotine concentrations rise slowly to an average of 6 ng/mL in contrast to those of a cigarette, which increase rapidly and reach a mean Cmax of approximately 49 ng/mL within 5 minutes.

The temperature dependency of nicotine release from the NICOTROL Inhaler was studied between 68°F and 104°F in eighteen patients. Average achievable steady state plasma levels after 20 minutes of an intensive inhalation regimen each hour at ambient room temperature are on the order of 23 ng/mL. The corresponding nicotine plasma levels achievable at 86°F and 104°F are on the order of 30 and 34 ng/mL. Nicotine peak plasma concentration (Cmax) at steady-state, after 20 minutes of an intensive inhalation regimen per hour, for 10 hours.

 | Cmax (ng/mL)
 | 20°C /68°F | 30°C /86°F | 40°C/104°F
 | N=18 | N=18 | N=18
Mean | 22.5 | 29.7 | 34.0
S.D. | 7.7 | 8.3 | 6.9
Min | 11.1 | 17.6 | 24.1
Max | 40.4 | 47.2 | 48.6

Ad libitum use of the NICOTROL Inhaler typically produces nicotine plasma levels of 6–8 ng/mL, corresponding to about 1/3 of those achieved with cigarette smoking.

Distribution

The volume of distribution following IV administration of nicotine is approximately 2 to 3 L/kg. Plasma protein binding of nicotine is <5%. Therefore, changes in nicotine binding from use of concomitant drugs or alterations of plasma proteins by disease states would not be expected to have significant effects on nicotine kinetics.

Metabolism

More than 20 metabolites of nicotine have been identified, all of which are less active than the parent compound. The primary urinary metabolites are cotinine (15% of the dose) and trans-3-hydroxycotinine (45% of the dose). Cotinine has a half-life of 15 to 20 hours and concentrations that exceed nicotine by 10-fold. The major site for the metabolism of nicotine is the liver. The kidney and lung are also sites of nicotine metabolism.

Elimination

About 10% of the nicotine absorbed is excreted unchanged in the urine. This may be increased to up to 30% with high urine flow rates and urinary acidification below pH 5. The average plasma clearance is about 1.2 L/min in a healthy adult smoker. The apparent elimination half-life of nicotine is 1 to 2 hours.

Gender Differences

Intersubject variability coefficients of variation (C.V.) for the pharmacokinetic parameters (AUC and Cmax) were approximately 40% and 30% respectively, for males and females. There were no medically significant differences between females and males in the kinetics of NICOTROL Inhaler.

CLINICAL TRIALS

The efficacy of NICOTROL Inhaler therapy as an aid to smoking cessation was demonstrated in two single-center, placebo-controlled, double-blind trials with a total of 445 healthy patients. The number of NICOTROL Inhaler cartridges used was a minimum dose of 4 cartridges/day and a maximum dose of 20 cartridges/day. In both studies, the recommended duration of treatment was 3 months; however, the patients were permitted to continue to use the product for up to 6 months, if they wished. The quit rates are the percentage of all persons initially enrolled who continuously abstained after week 2. NICOTROL Inhaler was more effective than placebo at 6 weeks, 3 months and 6 months. The efficacy is shown in the following table.

Quit Rates by Treatment
(N= 445 Patients in 2 Studies)
Group | Number of Patients | At 6 Weeks | At 3 Months | At 6 Months | At 12 Months [Follow-up, patients not on treatment.]
Nicotrol Inhaler | 223 | 44–45% | 31–32% | 20–21% | 11–13%
Placebo | 222 | 14–23% | 8–15% | 6–11% | 5–10%

Patients who used NICOTROL Inhaler had a significant reduction in the "urge to smoke", a major nicotine withdrawal symptom, compared with placebo-treated patients throughout the first week, (see Figure 1).

INDICATIONS AND USAGE

NICOTROL Inhaler is indicated as an aid to smoking cessation for the relief of nicotine withdrawal symptoms. NICOTROL Inhaler therapy is recommended for use as part of a comprehensive behavioral smoking cessation program.

CONTRAINDICATIONS

Use of NICOTROL Inhaler therapy is contraindicated in patients with known hypersensitivity or allergy to nicotine or to menthol.

WARNINGS

Nicotine from any source can be toxic and addictive. Smoking causes lung disease, cancer and heart disease, and may adversely affect pregnant women or the fetus. For any smoker, with or without concomitant disease or pregnancy, the risk of nicotine replacement in a smoking cessation program should be weighed against the hazard of continued smoking, and the likelihood of achieving cessation of smoking without nicotine replacement.

Pregnancy, Warning

Tobacco smoke, which has been shown to be harmful to the fetus, contains nicotine, hydrogen cyanide, and carbon monoxide. The NICOTROL Inhaler does not deliver hydrogen cyanide and carbon monoxide. However, nicotine has been shown in animal studies to cause fetal harm. It is therefore presumed that NICOTROL Inhaler can cause fetal harm when administered to a pregnant woman. The effect of nicotine delivery by NICOTROL Inhaler has not been examined in pregnancy (See PRECAUTIONS). Therefore, pregnant smokers should be encouraged to attempt cessation using educational and behavioral interventions before using pharmacological approaches. If NICOTROL Inhaler is used during pregnancy, or if the patient becomes pregnant while using it, the patient should be apprised of the potential hazard to the fetus.

Safety Note Concerning Children

This product contains nicotine and should be kept out of the reach of children and pets. The amounts of nicotine that are tolerated by adult smokers can produce symptoms of poisoning and could prove fatal if the nicotine from the NICOTROL Inhaler is inhaled, ingested, or buccally absorbed by children or pets. A cartridge contains about 60% of its initial drug content when it is discarded, which is about 6 mg. Patients should be cautioned to keep both the used and unused cartridges of NICOTROL Inhaler out of the reach of children and pets.

All components of the NICOTROL Inhaler system should also be kept out of the reach of children and pets to avoid accidental swallowing and choking.

PRECAUTIONS

General

The patient should be urged to stop smoking completely when initiating NICOTROL Inhaler therapy (See DOSAGE AND ADMINISTRATION). Patients should be informed that if they continue to smoke while using the product, they may experience adverse effects due to peak nicotine levels higher than those experienced from smoking alone. If there is a clinically significant increase in cardiovascular or other effects attributable to nicotine, the treatment should be discontinued (See WARNINGS). Physicians should anticipate that concomitant medications may need dosage adjustment (See Drug Interactions). Sustained use (beyond 6 months) of NICOTROL Inhaler by patients who stop smoking has not been studied and is not recommended. (See DRUG ABUSE AND DEPENDENCE).

Bronchospastic Disease

NICOTROL Inhaler has not been specifically studied in asthma or chronic pulmonary disease. Nicotine is an airway irritant and might cause bronchospasm. NICOTROL Inhaler should be used with caution in patients with bronchospastic disease. Other forms of nicotine replacement might be preferable in patients with severe bronchospastic airway disease.

Cardiovascular or Peripheral Vascular Diseases

The risks of nicotine replacement in patients with cardiovascular and peripheral vascular diseases should be weighed against the benefits of including nicotine replacement in a smoking cessation program for them. Specifically, patients with coronary heart disease (history of myocardial infarction and/or angina pectoris), serious cardiac arrhythmias, or vasospastic diseases (Buerger's disease, Prinzmetal's variant angina and Raynaud's phenomena) should be evaluated carefully before nicotine replacement is prescribed.

Tachycardia and palpitations have been reported occasionally with the use of NICOTROL Inhaler as well as with other nicotine replacement therapies. No serious cardiovascular events were reported in clinical studies with NICOTROL Inhaler, but if such symptoms occur, its use should be discontinued.

NICOTROL Inhaler generally should not be used in patients during the immediate post-myocardial infarction period, nor in patients with serious arrhythmias, or with severe or worsening angina.

Renal or Hepatic Insufficiency

The pharmacokinetics of nicotine have not been studied in the elderly or in patients with renal or hepatic impairment. However, given that nicotine is extensively metabolized and that its total system clearance is dependent on liver blood flow, some influence of hepatic impairment on drug kinetics (reduced clearance) should be anticipated. Only severe renal impairment would be expected to affect the clearance of nicotine or its metabolites from the circulation (See PHARMACOKINETICS).

Endocrine Diseases

NICOTROL Inhaler therapy should be used with caution in patients with hyperthyroidism, pheochromocytoma or insulin-dependent diabetes, since nicotine causes the release of catecholamines by the adrenal medulla.

Peptic Ulcer Disease

Nicotine delays healing in peptic ulcer disease; therefore, NICOTROL Inhaler therapy should be used with caution in patients with active peptic ulcers and only when the benefits of including nicotine replacement in a smoking cessation program outweigh the risks.

Accelerated Hypertension

Nicotine therapy constitutes a risk factor for development of malignant hypertension in patients with accelerated hypertension; therefore, NICOTROL Inhaler therapy should be used with caution in these patients and only when the benefits of including nicotine replacement in a smoking cessation program outweigh the risks.

Information for Patient

A patient information sheet is included in the package of NICOTROL Inhaler cartridges dispensed to the patient. Patients should be encouraged to read the information sheet carefully and to ask their physician and pharmacist about the proper use of the product (See DOSAGE AND ADMINISTRATION). Patients must be advised to keep both used and unused cartridges out of the reach of children and pets.

Drug Interactions

Physiological changes resulting from smoking cessation, with or without nicotine replacement, may alter the pharmacokinetics of certain concomitant medications, such as tricyclic antidepressants and theophylline. Doses of these and perhaps other medications may need to be adjusted in patients who successfully quit smoking.

Carcinogenesis, Mutagenesis, Impairment of Fertility

Nicotine itself does not appear to be a carcinogen in laboratory animals. However, nicotine and its metabolites increased the incidences of tumors in the cheek pouches of hamsters and forestomach of F344 rats, respectively when given in combination with tumor-initiators. One study, which could not be replicated, suggested that cotinine, the primary metabolite of nicotine, may cause lymphoreticular sarcoma in the large intestine of rats. Neither nicotine nor cotinine was mutagenic in the Ames salmonella test. Nicotine induced reparable DNA damage in an E. coli test system. Nicotine was shown to be genotoxic in a test system using Chinese hamster ovary cells. In rats and rabbits, implantation can be delayed or inhibited by a reduction in DNA synthesis that appears to be caused by nicotine. Studies have shown a decrease in litter size in rats treated with nicotine during gestation.

PREGNANCY

Pregnancy Category D

(See WARNINGS sections). The harmful effects of cigarette smoking on maternal and fetal health are clearly established. These include low birth weight, an increased risk of spontaneous abortion, and increased perinatal mortality. The specific effects of NICOTROL Inhaler therapy on fetal development are unknown. Therefore pregnant smokers should be encouraged to attempt cessation using educational and behavioral interventions before using pharmacological approaches.

Spontaneous abortion during nicotine replacement therapy has been reported; as with smoking, nicotine as a contributing factor cannot be excluded.

NICOTROL Inhaler therapy should be used during pregnancy only if the likelihood of smoking cessation justifies the potential risk of using it by the pregnant patient, who might continue to smoke.

Teratogenicity

Animal Studies

Nicotine was shown to produce skeletal abnormalities in the offspring of mice when toxic doses were given to the dams (25 mg/kg IP or SC).

Human Studies

Nicotine teratogenicity has not been studied in humans except as a component of cigarette smoke (each cigarette smoked delivers about 1 mg of nicotine). It has not been possible to conclude whether cigarette smoking is teratogenic to humans.

Other Effects

Animal Studies

A nicotine bolus (up to 2 mg/kg) to pregnant rhesus monkeys caused acidosis, hypercarbia, and hypotension (fetal and maternal concentrations were about 20 times those achieved after smoking one cigarette in 5 minutes). Fetal breathing movements were reduced in the fetal lamb after intravenous injection of 0.25 mg/kg nicotine to the ewe (equivalent to smoking 1 cigarette every 20 seconds for 5 minutes). Uterine blood flow was reduced about 30% after infusion of 0.1 µg/kg/min nicotine to pregnant rhesus monkeys (equivalent to smoking about six cigarettes every minute for 20 minutes).

Human Experience

Cigarette smoking during pregnancy is associated with an increased risk of spontaneous abortion, low birth weight infants and perinatal mortality. Nicotine and carbon monoxide are considered the most likely mediators of these outcomes. The effects of cigarette smoking on fetal cardiovascular parameters have been studied near term. Cigarettes increased fetal aortic blood flow and heart rate and decreased uterine blood flow and fetal breathing movements. NICOTROL Inhaler therapy has not been studied in pregnant women.

Labor and Delivery

NICOTROL Inhaler is not recommended for use during labor and delivery. The effect of nicotine on a mother or the fetus during labor is unknown.

Use in Nursing Mothers

Caution should be exercised when the NICOTROL Inhaler is administered to nursing mothers. The safety of NICOTROL Inhaler therapy in nursing infants has not been examined. Nicotine passes freely into breast milk; the milk to plasma ratio averages 2.9. Nicotine is absorbed orally. An infant has the ability to clear nicotine by hepatic first-pass clearance; however, the efficiency of removal is probably lowest at birth. Nicotine concentrations in milk can be expected to be lower with NICOTROL Inhaler when used as recommended than with cigarette smoking, as maternal plasma nicotine concentrations are generally reduced with nicotine replacement. The risk of exposure of the infant to nicotine from NICOTROL Inhaler therapy should be weighed against the risks associated with the infant's exposure to nicotine from continued smoking by the mother (passive smoke exposure and contamination of breast milk with other components of tobacco smoke) and from the NICOTROL Inhaler alone, or in combination with continued smoking.

Pediatric Use

Safety and effectiveness in pediatric and adolescent patients below the age of 18 years have not been established for any nicotine replacement product. However, no specific medical risk is known or expected in nicotine dependent adolescents. NICOTROL Inhaler should be used for the treatment of tobacco dependence in the older adolescent only if the potential benefit justifies the potential risk.

Geriatric Use

Clinical studies of NICOTROL Inhaler did not include sufficient numbers of subjects age 65 and over to determine whether they respond differently from younger subjects. Other reports on clinical experience have not identified differences between older and younger patients. In general, dosage selection for an elderly patient should be cautious, usually starting at the low end of the dosage range reflecting the greater frequency of decreased hepatic, renal, or cardiac function, and of concomitant disease.

ADVERSE REACTIONS

Assessment of adverse events in the 1,439 patients (730 on active drug) who participated in controlled clinical trials (including three dose finding studies) is complicated by the occurrence of signs and symptoms of nicotine withdrawal in some patients and nicotine excess in others. The incidence of adverse events is confounded by: (1) the many minor complaints that smokers commonly have, (2) continued smoking by many patients and (3) the local irritation from both the active drug and the placebo.

Local Irritation

NICOTROL Inhaler and the placebo were both associated with local irritant side effects. Local irritation in mouth and throat was reported by 40% of patients on active drug as compared to 18% of patients on placebo. Irritant effects were higher in the two pivotal trials with higher doses being 66% on active drug and 42% on placebo. Coughing (32% active versus 12% placebo) and rhinitis (23% active versus 16% placebo) were also higher on active drug. The majority of patients rated these symptoms as mild. The frequency of cough, and mouth and throat irritation declined with continued use of NICOTROL Inhaler. Other adverse events that occurred in over 3% of patients on active drug in placebo controlled pivotal trials considered possibly related to the local irritant effects of the NICOTROL Inhaler are taste comments, pain in jaw and neck, tooth disorders and sinusitis.

Withdrawal

Symptoms of withdrawal were common in both active and placebo groups. Common withdrawal symptoms seen in over 3% of patients on active drug included: dizziness, anxiety, sleep disorder, depression, withdrawal syndrome, drug dependence, fatigue and myalgia.

Nicotine-Related Adverse Events

The most common nicotine-related adverse event was dyspepsia. This was present in 18% of patients in the active group compared to 9% of patients in the placebo group. Other nicotine related events present in greater than 3% of patients on active drug include nausea, diarrhea, and hiccup.

Smoking related adverse events present in greater than 3% of patients on active drug include chest discomfort, bronchitis, and hypertension.

Other Adverse Events

Adverse events of unknown relationship to nicotine occurring in greater than 3% of patients on active drug include headache (26% of patients on active and 15% of patients on placebo), influenza-like symptoms, pain, back-pain, allergy, paresthesias, flatulence and fever.

DRUG ABUSE AND DEPENDENCE

NICOTROL Inhaler is likely to have a low abuse potential based on differences between the product and cigarettes in three characteristics commonly considered important in contributing to abuse: slower absorption, smaller fluctuations in blood levels and lower blood levels of nicotine. NICOTROL Inhaler, like many other nicotine-based smoking cessation therapies, does not produce arterial concentrations similar to cigarettes. However, nicotine withdrawal symptoms were noted in clinical trials at the time of NICOTROL Inhaler tapering and after NICOTROL Inhaler discontinuation.

Dependence might occur from transference of tobacco-related nicotine dependence to the NICOTROL Inhaler. The use of the inhaler beyond 6 months has not been evaluated in clinical trials and is not recommended. To minimize the risk of dependence, patients should be encouraged to withdraw gradually from NICOTROL Inhaler therapy after 3 months of usage (See DOSAGE AND ADMINISTRATION). If necessary, dose reduction can be achieved by gradual reduction of the dose over a 6 to 12 week period.

OVERDOSAGE

Signs and Symptoms of Nicotine Toxicity

Signs and symptoms of an overdose of the NICOTROL Inhaler would be expected to be the same as those of acute nicotine poisoning including: pallor, cold sweat, nausea, salivation, vomiting, abdominal pain, diarrhea, headache, dizziness, disturbed hearing and vision, tremor, mental confusion, and weakness. Prostration, hypotension, and respiratory failure may ensue with large overdoses. Lethal doses produce convulsions quickly and death follows as a result of peripheral or central respiratory paralysis or, less frequently, cardiac failure.

Overdose from Inhalation

The oral LD50 for nicotine is >5 mg/kg in dogs and >24 mg/kg in rodents. Death is due to respiratory paralysis. The oral minimum acute lethal dose for nicotine in adult humans is reported to be 40 to 60 mg (<1 mg/kg). The effects of using several cartridges in rapid succession are unknown (See WARNINGS, Safety Note Concerning Children).

One cartridge of NICOTROL Inhaler contains 10 mg nicotine, of which, approximately 4 mg is delivered nicotine. It is unlikely that an excessive nicotine overdose will occur via inhalation. Should such an overdose occur, however, with signs of nicotine poisoning, the patient should be instructed to contact his/her physician immediately. For additional emergency information, call your regional poison center or call the National Capital Poison Center toll free (1-800-222-1222).

Overdose from Ingestion

Persons ingesting NICOTROL Inhaler cartridges should be referred to a health care facility for management. In unconscious patients with a secure airway, instill activated charcoal via a nasogastric tube. A saline cathartic or sorbitol may be added to the first dose of activated charcoal. Repeated doses of activated charcoal should be administered as long as the cartridge remains in the gastrointestinal tract since it will continue to release nicotine for many hours. The NICOTROL Inhaler cartridges can be identified with a radiogram.

Management of Nicotine Poisoning

Other supportive measures include diazepam or barbiturates for seizures, atropine for excessive bronchial secretions or diarrhea, respiratory support for respiratory failure, and vigorous fluid support for hypotension and cardiovascular collapse.

DOSAGE AND ADMINISTRATION

Patients must desire to stop smoking and should be instructed to stop smoking completely as they begin using NICOTROL Inhaler. It is important that patients understand the instructions, and have their questions answered. They should clearly understand the directions for using the NICOTROL Inhaler and safely disposing of the used cartridges.

The initial dosage of NICOTROL Inhaler is individualized. Patients may selftitrate to the level of nicotine they require. Most successful patients in the clinical trials used between 6 and 16 cartridges a day. Best effect was achieved by frequent continuous puffing (20 minutes). The recommended duration of treatment is 3 months, after which patients may be weaned from the NICOTROL Inhaler by gradual reduction of the daily dose over the following 6 to 12 weeks. The safety and efficacy of the continued use of NICOTROL Inhaler for periods longer than 6 months have not been studied and such use is not recommended.

Dosing recommendations are summarized in the table below.

RECOMMENDED DOSING

 | Duration | Recommended Cartridges/day
INITIAL TREATMENT | Up to 12 Weeks | 6 – 16
Gradual Reduction (if needed) | 6–12 Weeks | No tapering strategy has been shown to be superior to any other in clinical studies.

Initial Treatment (Up to 12 Weeks)

For best results, patients should be encouraged to use at least 6 cartridges per day at least for the first 3 to 6 weeks of treatment. In clinical trials, the average daily dose was >6 (range 3 to 18) cartridges for patients who successfully quit smoking. Additional doses may be needed to control the urge to smoke with a maximum of 16 cartridges daily for up to 12 weeks. Regular use of NICOTROL Inhaler during the first week of treatment may help patients adapt to the irritant effects of the product. Some patients may exhibit signs or symptoms of nicotine withdrawal or excess which will require an adjustment of the dosage (see Individualization of Dosage).

Gradual Reduction of Dose (Up to 12 Weeks)

Most patients will need to gradually discontinue the use of NICOTROL Inhaler after the initial treatment period. Gradual reduction of dose may begin after twelve weeks of initial treatment and may last for up to twelve weeks. Recommended strategies for discontinuing use include suggesting to patients that they use the product less frequently, keep a tally of daily usage, try to meet a steadily reducing target or set a planned quit date for stopping use of the product.

Individualization of Dosage

The NICOTROL Inhaler provides the smoker with adequate amounts of nicotine to reduce the urge to smoke, and may provide some degree of comfort by providing a hand-to-mouth ritual similar to smoking, although the importance of such an effect in smoking cessation is, as yet, unknown.

The success or failure of smoking cessation is influenced by the quality, intensity and frequency of supportive care. Patients are more likely to quit smoking if they are seen frequently and participate in formal smoking cessation programs.

The goal of NICOTROL Inhaler therapy is complete abstinence. If a patient is unable to stop smoking by the fourth week of therapy, treatment should probably be discontinued.

Patients who fail to quit on any attempt may benefit from interventions to improve their chances for success on subsequent attempts. Patients who were unsuccessful should be counseled and should then probably be given a therapeutic holiday before the next attempt. A new quit attempt should be encouraged when conditions are more favorable.

Based on the clinical trials, a reasonable approach to assisting patients in their attempt to quit smoking is to begin initial treatment, using the recommended dosage (See DOSAGE AND ADMINISTRATION). Dosage can then be adjusted in those patients with signs or symptoms of nicotine withdrawal or excess. Patients who are successfully abstinent on NICOTROL Inhaler should be treated at the selected dosage for up to 12 weeks, after which use of the Inhaler should be gradually reduced over the next 6 to 12 weeks. Some patients may not require gradual reduction of dosage and may abruptly stop treatment successfully. The safe use of this product for longer than 6 months has not been established.

The symptoms of nicotine withdrawal overlap those of nicotine excess (See Pharmacodynamics and ADVERSE REACTIONS sections). Since patients using NICOTROL Inhaler may also smoke intermittently, it is sometimes difficult to determine if they are experiencing nicotine withdrawal or nicotine excess. Controlled clinical trials of nicotine products suggest that palpitations, nausea and sweating are more often symptoms of nicotine excess, whereas anxiety, nervousness and irritability are more often symptoms of nicotine withdrawal.

SAFETY AND HANDLING

Disposal

See patient information sheet for instructions on handling and disposal. After using the NICOTROL Inhaler, carefully separate the mouthpiece, remove the used cartridge and throw it away, out of the reach of children and pets. Store the mouthpiece in the plastic storage case for further use. The mouthpiece is reusable and should be cleaned regularly with soap and water. The NICOTROL Inhaler cartridges can be detected on a radiogram.

How Supplied

NICOTROL INHALER (nicotine inhalation system) is supplied as 168 cartridges each containing 10 mg (4 mg is delivered) nicotine (NDC 54868-5052-0). Each unit consists of 5 mouthpieces, 28 storage trays each containing 6 cartridges and 1 plastic storage case. A patient information leaflet is enclosed with the package.

Store at room temperature not to exceed 77°F (25°C).
Protect cartridges from light.

Rx only

Relabeling of "Additional" barcode label by:
Physicians Total Care, Inc.
Tulsa, OK 74146

PATIENT INFORMATION

Nicotrol® Inhaler
(nicotine inhalation system)
10 mg per cartridge
(4 mg delivered)

An Aid to Help You Stop Smoking

Patient Information

Read and follow carefully.
If you have questions or want more information, ask your doctor or pharmacist.

1. NICOTROL Inhaler helps you quit smoking by reducing your urge to smoke. Success in quitting with nicotine replacement therapy (such as NICOTROL Inhaler) usually involves behavior change.
  - Your doctor may adjust the number of Inhaler cartridges during the first few weeks. As your body adjusts to not smoking, your doctor will either tell you to stop using the Inhaler or slowly reduce the dose.
  - People who use Nicotrol Inhaler with a comprehensive behavioral smoking cessation program are more successful in quitting smoking. This program can include support groups, counseling or specific behavior change techniques.

2. Side Effects: Many people experience mild irritation of the mouth or throat and cough when they first use the Nicotrol Inhaler. Most people get used to these effects in a short time. Stomach upset may also occur.
3. Because you are already addicted to the nicotine in cigarettes, it is possible to stay dependent on the lower dose of nicotine found in the Nicotrol Inhaler. It is important to use the Inhaler for only as long as directed by your doctor to overcome your nicotine addiction and smoking habit.

1. Commit yourself - NO SMOKING! For the NICOTROL Inhaler to help, you must be firmly committed to quitting! Stop smoking as soon as you start using the Inhaler. Do not smoke or use any other tobacco products at any time while using the NICOTROL Inhaler.
  - Nicotine overdose can occur. If symptoms of overdose occur, call a doctor or Poison Control Center immediately. Overdose symptoms include: bad headaches, dizziness, upset stomach, drooling, vomiting, diarrhea, cold sweat, blurred vision, hearing difficulties, mental confusion, weakness and fainting.

2. Keep out of reach of children and pets. The NICOTROL Inhaler can cause serious illness in children and pets - even in very small amounts. If a child chews on or swallows NICOTROL Inhaler cartridges, call a doctor or Poison Control Center. After a cartridge is used, throw away out of reach of children and pets. Even used cartridges contain enough nicotine to seriously harm children and pets.
  The NICOTROL Inhaler is a child resistant product. Please read carefully the instructions regarding how to open, close and lock.

3. Tell your doctor if you have:

• | heart problems (recent heart attack, | • | high blood pressure
 | irregular heartbeat, severe or | • | allergies to drugs
 | worsening heart pain) | • | diabetes requiring insulin
• | stomach ulcers | • | kidney or liver disease
• | overactive thyroid | • | wheezing or asthma
• | Tell your doctor about any medicines you are taking– the dosages may need to be changed. Check with your doctor before taking any new medicine while using NICOTROL Inhaler.

4. If you are pregnant or breast-feeding, only use this medicine on the advice of your health care provider. Smoking can seriously harm your child. Try to stop smoking without using any nicotine replacement medicine. This medicine is believed to be safer than smoking. However, the risks to your child from this medicine are not fully known.

1.
  - Follow doctor's directions.
  - Stop smoking completely during the NICOTROL Inhaler treatment program.
2.
  - Remove mouthpiece from plastic wrap.
  - Push the top and bottom together and turn the two pieces to line up the markings.
  - Pull the top and bottom apart.
3.
  - Take out cartridge tray.
  - Peel back to release 1 cartridge.
  - Insert cartridge into Inhaler.
  - Push hard on the cartridge until it pops down into place.
4.
  - Line up the markings again and push the two pieces back together so they fit tight.
  - Turn the top and bottom pieces so the markings do not line up and it is locked again.
  - Store cartridges in plastic case when not in use.
5.
  - Inhale deeply into back of throat or puff in short breaths.
  - As you inhale or puff through the mouthpiece, nicotine turns into a vapor and is absorbed into your mouth and throat.
  - Use Inhaler longer and more often at first to help control cigarette cravings.
6.
  - Nicotine in cartridges is used up after about 20 minutes of active puffing.
  - Try different schedules to help control cravings. Puffing on the Inhaler for 5 min. at a time will give you enough nicotine for 4 uses. In a few days you'll find what works best and know when nicotine in cartridges is used up.
  - Use Inhaler at room temperature (above 60°F), cold temperatures reduce amount of nicotine you inhale.
7.
  - When cartridge is empty, take off top of mouthpiece.
  - Throw used cartridge away, out of reach of children and pets.
  - When not in use keep the mouthpiece in the locked position and always store mouthpiece and cartridges in plastic case, out of reach of children and pets.
8.
  - Side Effects: You may experience mild irritation of the mouth or throat and cough when you first use the Nicotrol Inhaler. You should get used to these effects in a short time. Stomach upset may also occur.
  - Do not use more than 16 cartridges each day unless directed to do so by your doctor.
  - Do not use longer than 6 months.
  - Store cartridges at room temperature, not to exceed 77°F (25°C).
  - If you keep cartridges in car, be careful: interiors heat up quickly.
  - Protect from light.
  - Clean mouthpiece regularly with soap and water.

QUESTIONS? Call 1-888-642-6876

LAB-0345-3.0
December 2008

PRINCIPAL DISPLAY PANEL - 168 Cartridge Carton

NDC 54868-5052-0

Nicotrol® Inhaler
(nicotine inhalation
system)

10 mg/cartridge
(4 mg delivered)

Rx only

FOR ORAL INHALATION USE ONLY
KEEP OUT OF THE REACH OF CHILDREN

168 Cartridges
5 Mouthpieces, 1 Plastic Case